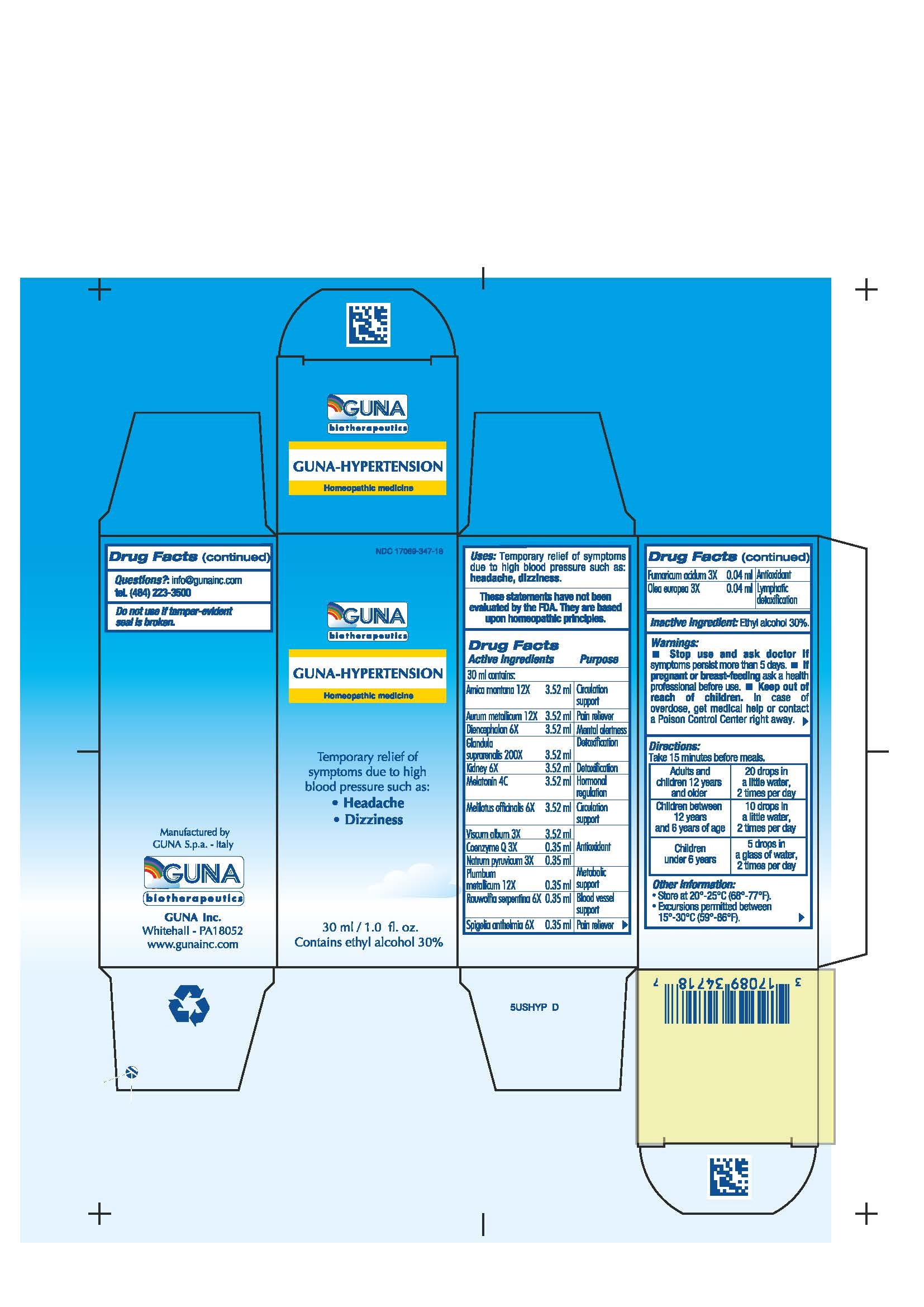 DRUG LABEL: GUNA-HYPERTENSION
NDC: 17089-347 | Form: SOLUTION/ DROPS
Manufacturer: Guna spa
Category: homeopathic | Type: HUMAN OTC DRUG LABEL
Date: 20181221

ACTIVE INGREDIENTS: ARNICA MONTANA 12 [hp_X]/30 mL; GOLD 12 [hp_X]/30 mL; UBIDECARENONE 3 [hp_X]/30 mL; SUS SCROFA DIENCEPHALON 6 [hp_X]/30 mL; FUMARIC ACID 3 [hp_X]/30 mL; SUS SCROFA ADRENAL GLAND 200 [hp_X]/30 mL; PORK KIDNEY 6 [hp_X]/30 mL; MELATONIN 4 [hp_C]/30 mL; MELILOTUS 6 [hp_X]/30 mL; SODIUM PYRUVATE 3 [hp_X]/30 mL; OLEA EUROPAEA FLOWER 3 [hp_X]/30 mL; LEAD 12 [hp_X]/30 mL; RAUWOLFIA SERPENTINA 6 [hp_X]/30 mL; SPIGELIA 6 [hp_X]/30 mL; VISCUM ALBUM FRUIT 3 [hp_X]/30 mL
INACTIVE INGREDIENTS: ALCOHOL 9 mL/30 mL

GUNA-HYPERTENSION

ACTIVE INGREDIENT

Arnica montana 12X Circulation support
Aurum metallicum 12X Pain reliever
Coenzyme Q 3X ANTIOXIDANT
Diencephalon 6X MENTAL ALERTNESS
Fumaricum acidum 3X ANTIOXIDANT
Glandula suprarenalis 200X DETOXIFICATION
Kidney 6X DETOXIFICATION
Melatonin 4C HORMONAL REGULATION
Melilotus officinalis 6X Circulation support
Natrum pyruvicum 3X ANTIOXIDANT
Olea europea 3X LYMPHATIC DETOXIFICATION
Plumbum metallicum 12X Metabolic support
Rauwolfia serpentina 6X BLOOD VESSEL SUPPORT
Spigelia anthelmia 6X Pain reliever
Viscum album 3X ANTIOXIDANT

PURPOSE

Temporary relief of symptoms due to high blood pressure such as:

- Headache
- Dizziness

- Stop use and ask doctor if symptoms persist more than 5 days.
- If pregnant or breast-feeding ask a health professional before use.
- Keep out of reach of children. In case of overdose, get medical help or contact a Poison Control Center right away.
- Contains ethyl alcohol 30%

PREGNANCY OR BREAST FEEDING

If pregnant or breast-feeding ask a doctor before use

Keep out of reach of children

DOSAGE AND ADMINISTRATION

Take 15 minutes before meals
Adults and children 12 years and older 20 drops in a little water, 2 times per day
Children between 12 years and 6 years of age 10 drops in a little water, 2 times per day
Children under 6 years Ask a doctor

Questions?: info@gunainc.com, tel. (484) 223-3500

INDICATIONS AND USAGE

Take 15 minutes before meals.

Inactive ingredient: Ethyl alcohol 30%.